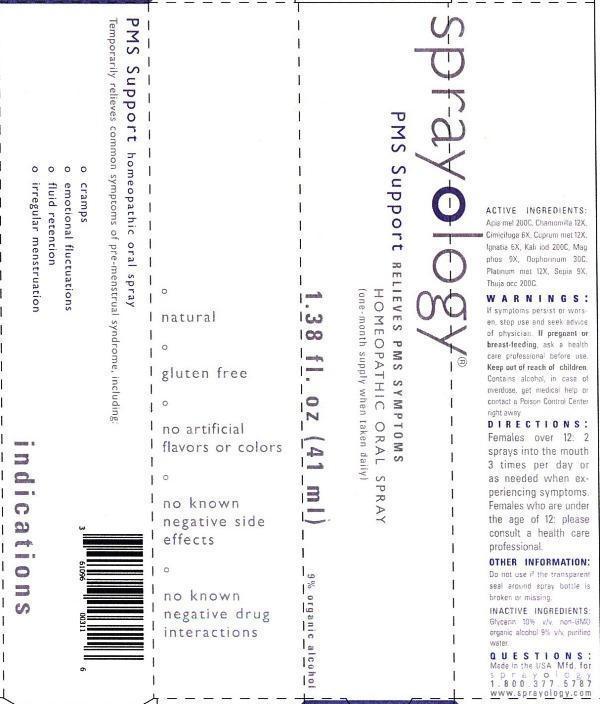 DRUG LABEL: Sprayology PMS Support
NDC: 61096-0031 | Form: LIQUID
Manufacturer: Eight and Company
Category: homeopathic | Type: HUMAN OTC DRUG LABEL
Date: 20140311

ACTIVE INGREDIENTS: APIS MELLIFERA 200 [hp_C]/41 mL; MATRICARIA RECUTITA 6 [hp_X]/41 mL; BLACK COHOSH 6 [hp_X]/41 mL; COPPER 12 [hp_X]/41 mL; STRYCHNOS IGNATII SEED 6 [hp_X]/41 mL; POTASSIUM IODIDE 200 [hp_C]/41 mL; MAGNESIUM PHOSPHATE, DIBASIC TRIHYDRATE 9 [hp_X]/41 mL; SUS SCROFA OVARY 30 [hp_C]/41 mL; PLATINUM 12 [hp_X]/41 mL; SEPIA OFFICINALIS JUICE 9 [hp_X]/41 mL; THUJA OCCIDENTALIS LEAFY TWIG 200 [hp_C]/41 mL
INACTIVE INGREDIENTS: GLYCERIN; ALCOHOL; WATER

Sprayology PMS Support

ACTIVE INGREDIENT

Active Ingredients: Apis mellifica 200C, Chamomilla 6X, Cimicifuga racemosa 6X, Cuprum metallicum 12X, Ignatia amara 6X, Kali iodatum 200C, Magnesia phosphorica 9X, Oophorinum 30C, Platinum metallicum 12X, Sepia 9X, Thuja occidentalis 200C.

WARNINGS

Warnings: If symptoms persist or worsen, stop use and seek advice of physician. If pregnant or breast-feeding, ask a health care professional before use. Keep out of reach of children. Contains alcohol, in case of overdose, get medical help or contact a Poison Control Center right away.

Keep out of reach of children.

Directions:

- Females over 12: 2 sprays into the mouth 3 times per day or as needed when experiencing symptoms.
- Females who are under the age of 12: please consult a health care professional.

PURPOSE

Temporarily relieves common symptoms of pre-menstrual syndrome, including:

- cramps
- emotional fluctuations
- fluid retention
- irregular menstruation

Other Information: Do not use if the transparent seal around spray bottle is broken or missing.

INACTIVE INGREDIENT

Inactive Ingredients: Glycerin 10% v/v, non-GMO organic alcohol 9% v/v and purified water.

INDICATIONS AND USAGE

Temporarily relieves common symptoms of pre-menstrual syndrome, including:

° cramps

° emotional fluctuations

° fluid retention

° irregular menstruation

° natural

° gluten free

° no artificial flavors or colors

° no known negative drug interactions